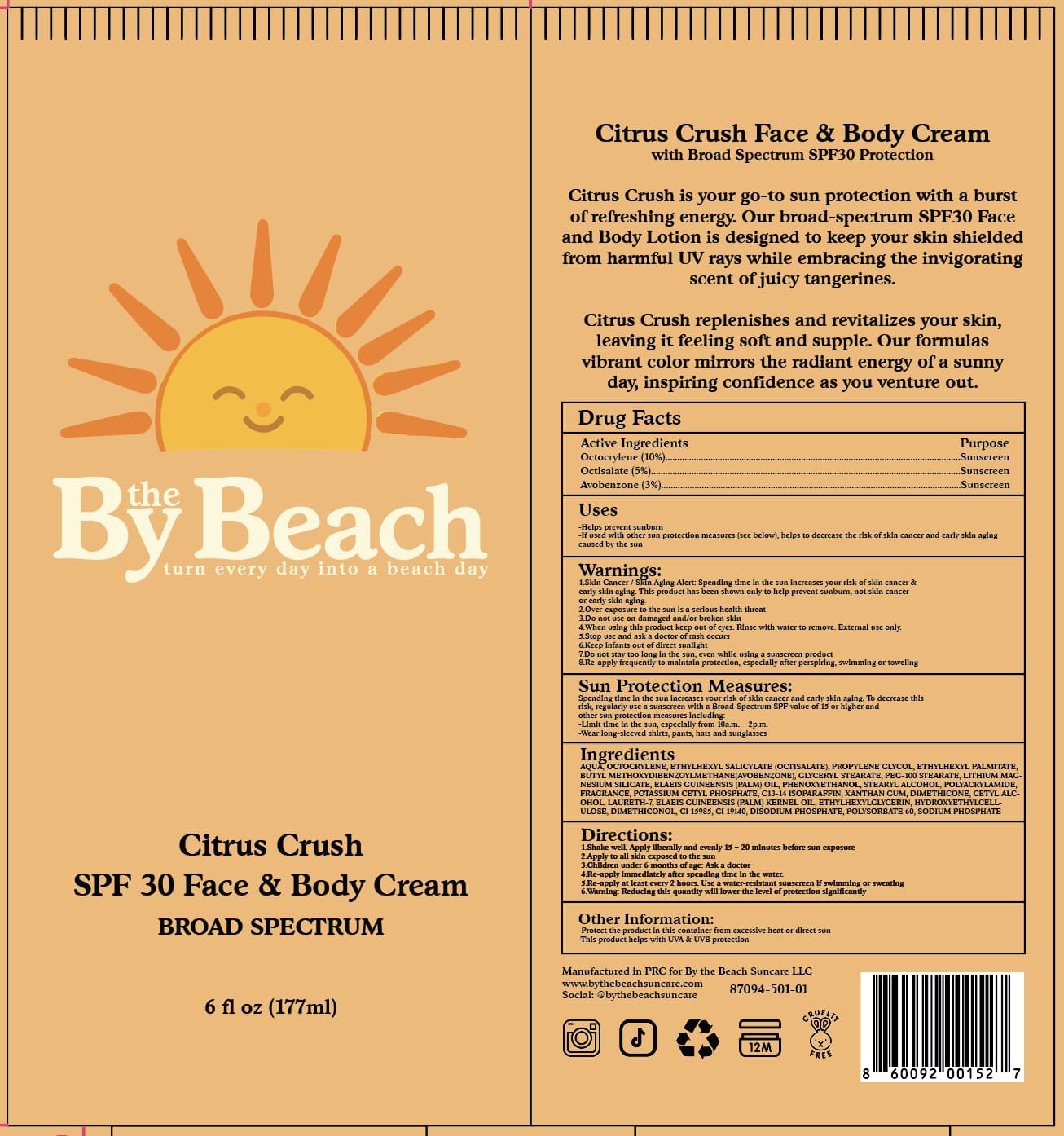 DRUG LABEL: By the Beach Suncare
NDC: 87094-111 | Form: CREAM
Manufacturer: By the Beach Suncare LLC
Category: otc | Type: HUMAN OTC DRUG LABEL
Date: 20251114

ACTIVE INGREDIENTS: OCTOCRYLENE 10 mg/100 mL; AVOBENZONE 3 mg/100 mL; OCTISALATE 5 mg/100 mL
INACTIVE INGREDIENTS: PEG-100 STEARATE; CETYL ALCOHOL; GLYCERYL STEARATE; LITHIUM MAGNESIUM SODIUM SILICATE; ELAEIS GUINEENSIS (PALM) OIL; POLYACRYLAMIDE (10000 MW); ETHYLHEXYL PALMITATE; CI 15985; PROPYLENE GLYCOL; C13-14 ISOPARAFFIN; HYDROXYETHYLCELLULOSE; CI 19140; PHENOXYETHANOL; STEARYL ALCOHOL; LAURETH-7; ETHYLHEXYLGLYCERIN; DIMETHICONOL (100000 CST); DISODIUM PHOSPHATE; POLYSORBATE 60; XANTHAN GUM; DIMETHICONE 1000; SODIUM PHOSPHATE; POTASSIUM CETYL PHOSPHATE; WATER

By The Beach-Guangzhou Citrus Crush 177 mL

Active Ingredient(s)

Octocrylene (10%) – Sunscreen

Octisalate (5%) – Sunscreen

Avobenzone (3%) – Sunscreen

Purpose

Sunscreen

Use

Helps prevent sunburn

If used with other sun protection measures (see below),

helps to decrease the risk of skin cancer and early skin aging caused by the sun

Warnings

Skin Cancer / Skin Aging Alert: Spending time in the sun increases your risk of skin cancer & early skin aging. This product has been shown only to help prevent sunburn, not skin cancer or early skin aging.

Over-exposure to the sun is a serious health threat

Do not use on damaged and/or broken skin

When using this product keep out of eyes. Rinse with water to remove. External use only.

Stop use and ask a doctor if rash occurs

Keep infants out of direct sunlight

Do not stay too long in the sun, even while using a sunscreen product

Re-apply frequently to maintain protection, especially after perspiring, swimming or toweling

Sun Protection Measures:
Spending time in the sun increases your risk of skin cancer and early skin aging. To decrease this risk, regularly use a sunscreen with a Broad-Spectrum SPF value of 15 or higher and other sun protection measures including:

Limit time in the sun, especially from 10 a.m. – 2 p.m.

Wear long-sleeved shirts, pants, hats and sunglasses

KEEP OUT OF REACH OF CHILDREN

Keep out of reach of childeren. Contact a Poison Control Center: This is the emergency contact for accidental overdose or ingestion

Directions

Shake well. Apply liberally and evenly 15 – 20 minutes before sun exposure

Apply to all skin exposed to the sun

Children under 6 months of age: Ask a doctor

Re-apply immediately after spending time in the water

Re-apply at least every 2 hours. Use a water-resistant sunscreen if swimming or sweating

Warning: Reducing this quantity will lower the level of protection significantly

Other information

Protect the product in this container from excessive heat or direct sun

This product helps with UVA & UVB protection

Inactive ingredients

AQUA, OCTOCRYLENE, ETHYLHEXYL SALICYLATE (OCTISALATE), PROPYLENE GLYCOL, ETHYLHEXYL PALMITATE, BUTYL METHOXYDIBENZOYLMETHANE (AVOBENZONE), GLYCERYL STEARATE, PEG-100 STEARATE, LITHIUM MAGNESIUM SILICATE, ELAEIS GUINEENSIS (PALM) OIL, PHENOXYETHANOL, STEARYL ALCOHOL, POLYACRYLAMIDE, FRAGRANCE, POTASSIUM CETYL PHOSPHATE, C13-14 ISOPARAFFIN, XANTHAN GUM, DIMETHICONE, CETYL ALCOHOL, LAURETH-7, ELAEIS GUINEENSIS (PALM) KERNEL OIL, ETHYLHEXYLGLYCERIN, HYDROXYETHYLCELLULOSE, DIMETHICONOL, CI 15985, CI 19140, DISODIUM PHOSPHATE, POLYSORBATE 60, SODIUM PHOSPHATE